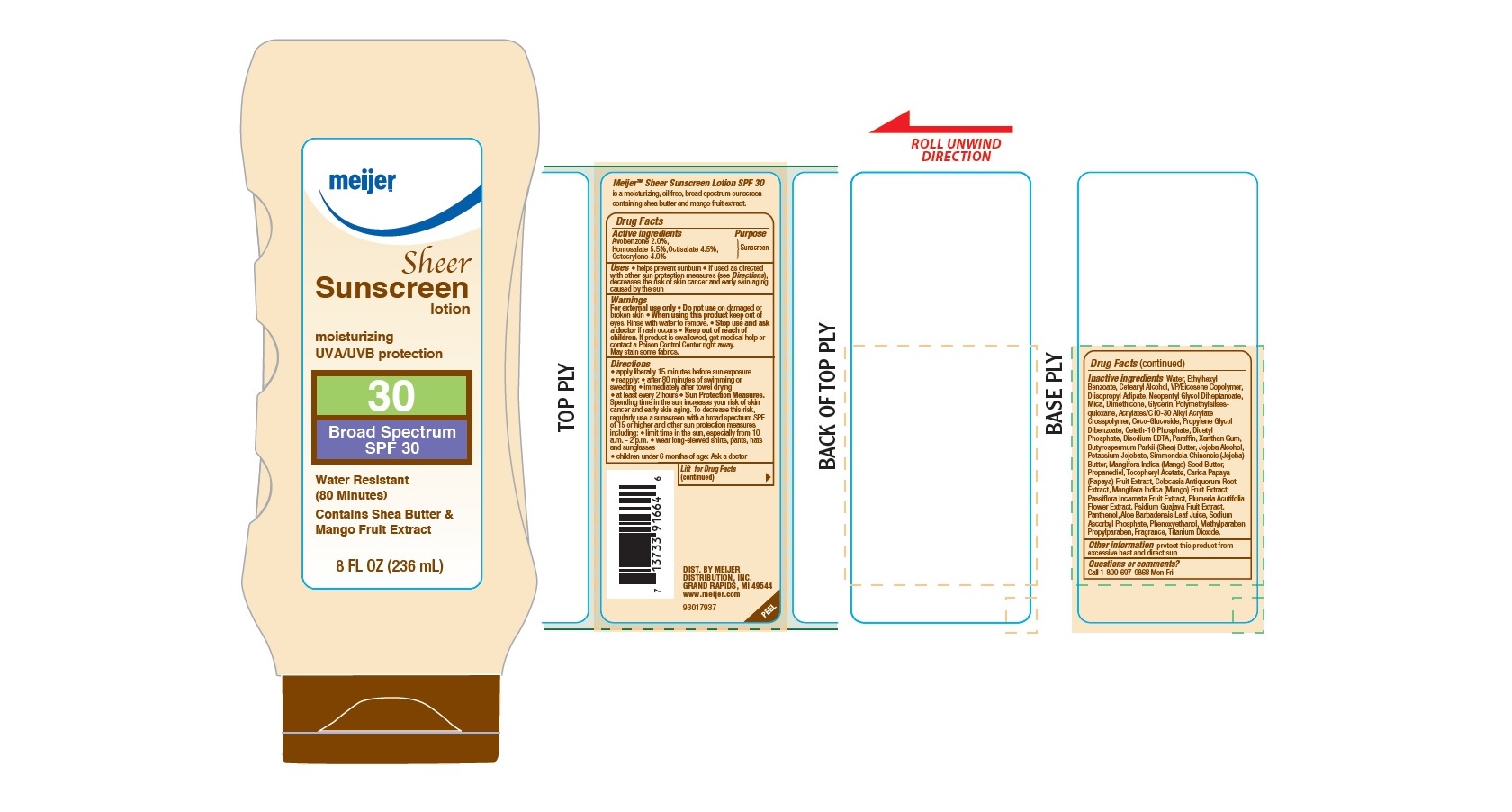 DRUG LABEL: Meijer Sheer Moisturing SPF 30
NDC: 41250-103 | Form: LOTION
Manufacturer: Meijer Distribution, Inc.
Category: otc | Type: HUMAN OTC DRUG LABEL
Date: 20160520

ACTIVE INGREDIENTS: AVOBENZONE 2 g/100 g; HOMOSALATE 5.5 g/100 g; OCTISALATE 4.5 g/100 g; OCTOCRYLENE 4 g/100 g
INACTIVE INGREDIENTS: WATER; 2-ETHYLHEXYL BENZOATE; CETOSTEARYL ALCOHOL; DIISOPROPYL ADIPATE; NEOPENTYL GLYCOL DIHEPTANOATE; MICA; DIMETHICONE; GLYCERIN; COCO GLUCOSIDE; PROPYLENE GLYCOL DIBENZOATE; CETETH-10 PHOSPHATE; DIHEXADECYL PHOSPHATE; EDETATE DISODIUM; PARAFFIN; XANTHAN GUM; SHEA BUTTER; JOJOBA BUTTER; MANGIFERA INDICA SEED BUTTER; PROPANEDIOL; .ALPHA.-TOCOPHEROL ACETATE; PAPAYA; COLOCASIA ESCULENTA ROOT; MANGO; PASSIFLORA INCARNATA FRUIT; PLUMERIA RUBRA FLOWER; GUAVA; PANTHENOL; ALOE VERA LEAF; SODIUM ASCORBYL PHOSPHATE; PHENOXYETHANOL; METHYLPARABEN; PROPYLPARABEN; TITANIUM DIOXIDE

Drub Facts

Active ingredients

Avobenzone 2.0%, Homosalate 5.5%, Octisalate 4.5%, Octocrylene 4.0%

Purpose

Sunscreen

Uses

• helps prevent sunburn

• if used as directed with other sun protection measures (see Directions), decreases the risk of skin cancer and early skin aging caused by the sun

Warnings

For external use only

Do not use

on damaged or broken skin

When using this product

keep out of eyes. Rinse with water to remove.

Stop use and ask a doctor

if rash occurs

Keep out of reach of children.

If product is swallowed, get medical help or contact a Poison Control Center right away.

• May stain some fabrics

Directions

• apply liberally 15 minutes before sun exposure

• reapply:

• after 80 minutes of swimming or sweating

• immediately after towel drying

• at least every 2 hours

• Sun Protection Measures: Spending time in the sun increases your risk of skin cancer and early skin aging. To decrease this risk, regularly use a sunscreen with a broad spectrum SPF of 15 or higher and other protection measures including:

• limit time in the sun, especially from 10 a.m. to 2 p.m.

• wear long-sleeved shirts, pants, hats, and sunglasses

• children under 6 months: Ask a doctor

Inactive ingredients

Water, Ethylhexyl Benzoate, Cetearyl Alcohol, VP/Eicosene Copolymer, Diisopropyl Adipate, Neopentyl Glycol Diheptanoate, Mica, Dimethicone, Glycerin, Polymethylsilsesquioxane, Acrylates/C10-30 Alkyl Acrylate Crosspolymer, Coco-Glucoside, Propylene Glycol Dibenzoate, Ceteth-10 Phosphate, Dicetyl Phosphate, Disodium EDTA, Paraffin, Xanthan Gum, Butyrospermum Parkii (Shea) Butter, Jojoba Alcohol, Potassium Jojobate, Simmondsia Chinensis (Jojoba) Butter, Mangifera Indica (Mango) Seed Butter, Propanediol, Tocopheryl Acetate, Carica Papaya (Papaya) Fruit Extract, Colocasia Antiquorum Root Extract, Mangifera Indica (Mango) Fruit Extract, Passiflora Incarnata Fruit Extract, Plumeria Acutifolia Flower Extract, Psidium Guajava Fruit Extract, Panthenol, Aloe Barbadensis Leaf Juice, Sodium Ascorbyl Phosphate, Phenoxyethanol, Methylparaben, Propylparaben, Fragrance, Titanium Dioxide.

Other information

protect this product from excessive heat and direct sun

Questions or comments?

Call 1-800-697-9868 Mon-Fri

Principal Display Panel

NDC 41250-103-56

meijer

Sheer Sunscreen Lotion

moisturizing

UVA/UVB protection

30

Broad Spectrum SPF 30

Water Resistant

(80 Minutes)

Contains Shea Butter and

Mango Fruit Extract

8 FL OZ (236 mL)